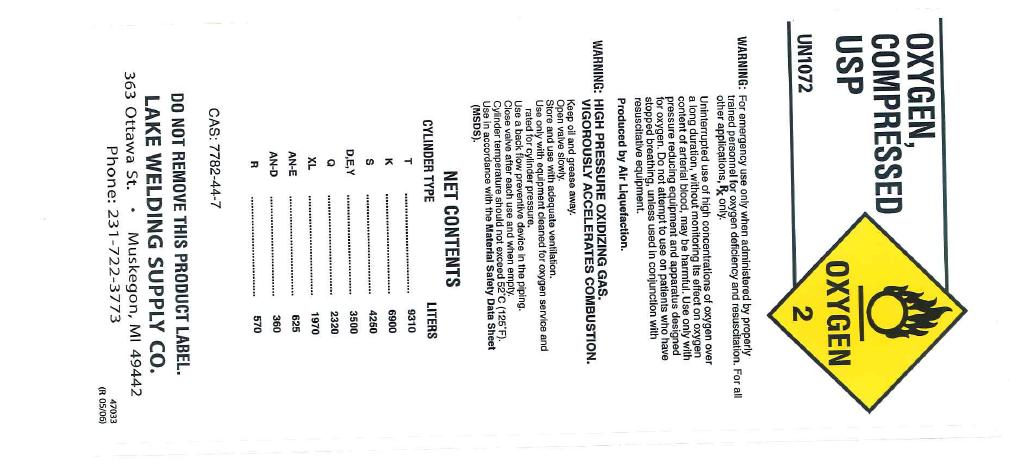 DRUG LABEL: Oxygen
NDC: 10641-001 | Form: GAS
Manufacturer: Lake Welding Supply Company
Category: prescription | Type: HUMAN PRESCRIPTION DRUG LABEL
Date: 20100608

ACTIVE INGREDIENTS: Oxygen 995 mL/1 L

oxygen

PACKAGE LABEL

OXYGEN, Compressed U.S.P. UN1072 OXYGEN 2
WARNING: For emergency use only when administered by properly trained personnel for oxygen deficiency and resuscitation. For all other medical applications, Rx ONLY. Uninterrupted use of high concentrations of oxygen over a long duration, without monitoring its effect on oxygen content of arterial blood, may be harmful. Use only with pressure reducing equipment and apparatus designed for use with oxygen. Do not attempt to use on patients who have stopped breathing unless used in conjunction with resuscitative equipment. Produced by Air Liquefaction.
WARNING: HIGH PRESSURE OXIDIZING GAS. VIGOROUSLY ACCELERATES COMBUSTION. Keep oil and grease away. Open valve slowly. Store and use with adequate ventilation. Use only with equipment cleaned for oxygen service and rated for cylinder pressure. Use a back flow preventive device in the piping. Close valve after each use and when empty. Cylinder temperature should not exceed 52 C (125F). Use in accordance with Material Safety Data Sheet (MSDS).
NET CONTENTS
CYLINDER TYPE LITERS
T 9310
K 6900
D,E,Y 3500
Q 2320
XL 1970
AN-E 625
AN-D 360
R 570
CAS: 7782-44-7
DO NOT REMOVE THIS PRODUCT LABEL.
LAKE WELDING SUPPLY CO. 363 Ottawa St. Muskegon, MI 49442 Phone: 231-722-3773
47033 (R 05/06)